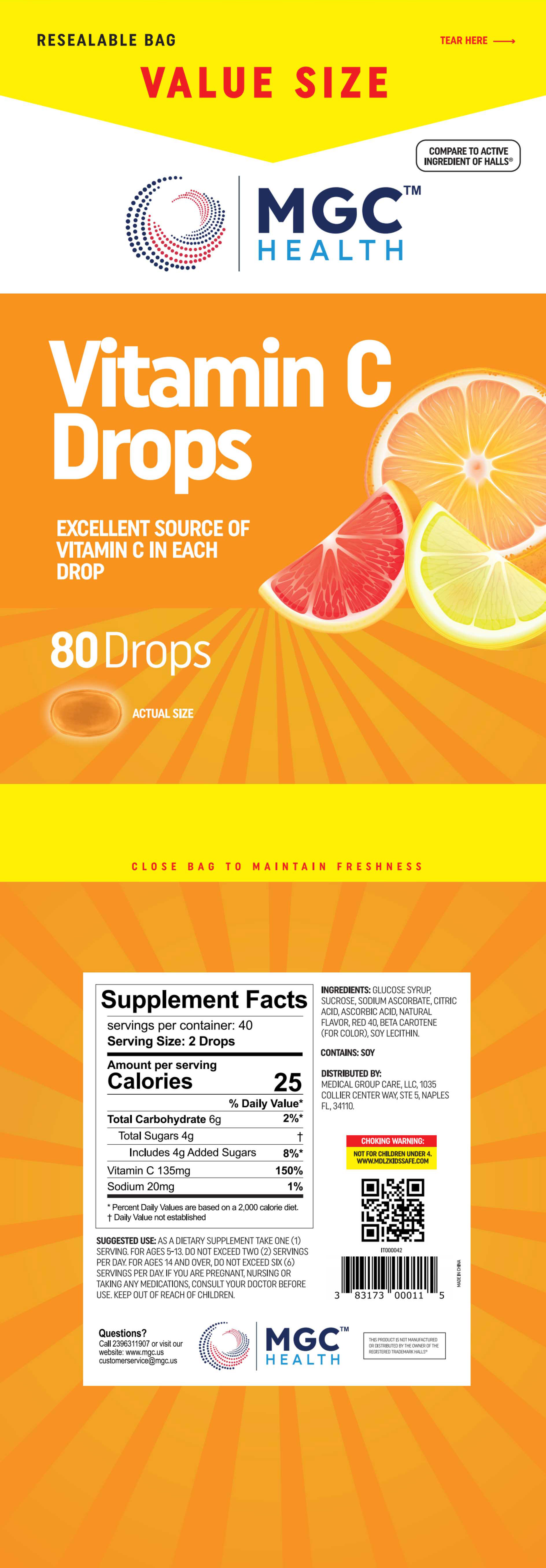 DRUG LABEL: Vitamin C Drops
NDC: 80404-601 | Form: TABLET, CHEWABLE, EXTENDED RELEASE
Manufacturer: Xinsanyang Pharmaceutical (Xiamen) Co., Ltd.
Category: otc | Type: HUMAN OTC DRUG LABEL
Date: 20230704

ACTIVE INGREDIENTS: ASCORBIC ACID 2.25 mg/100 mg
INACTIVE INGREDIENTS: CORN SYRUP; FD&C RED NO. 40; LECITHIN, SOYBEAN; SUCROSE; SODIUM ASCORBATE; BETA CAROTENE; CITRIC ACID MONOHYDRATE 0.6 mg/100 mg

Vitamin C Drops

Vitamin C Drops

ACTIVE INGREDIENT

ASCORBIC ACID(Vitamin C 135mg)

PURPOSE

AS A DIETARY SUPPLEMENT TAKE

INDICATIONS AND USAGE

SUGGESTED USE: AS A DIETARY SUPPLEMENT TAKE ONE(1)SERVING.FOR AGES 5-13. DO NOT EXCEED TWO (2) SERVINGSPER DAY FOR AGES 14 AND OVERDO NOT EXCEED SIX(6SERVINGS PER DAY IF YOU ARE PREGNANTNURSING ORTAKING ANY MEDICATIONSCONSULT YOUR DOCTOR BEFOREUSE.KEEP OUT OF REACH OF CHILDREN

WARNINGS

NOT FOR CHILDREN UNDER 4.

NOT FOR CHILDREN UNDER 4.

DO NOT EXCEED TWO (2) SERVINGSPER DAY FOR AGES 14 AND OVERDO
NOT EXCEED SIX(6)SERVINGS PER DAY
IF YOU ARE PREGNANTNURSING ORTAKING ANY MEDICATIONSCONSULT YOUR DOCTOR BEFOREUSE.

WHEN USING

SUGGESTED USE: AS A DIETARY SUPPLEMENT TAKE ONE(1)SERVING.FOR AGES 5-13.

STOP USE

NOT FOR CHILDREN UNDER 4.

KEEP OUT OF REACH OF CHILDREN

DOSAGE AND ADMINISTRATION

SUGGESTED USE: AS A DIETARY SUPPLEMENT TAKE ONE(1)SERVING.FOR AGES 5-13.
DO NOT EXCEED TWO (2) SERVINGSPER DAY FOR AGES 14 AND OVERDO
NOT EXCEED SIX(6)SERVINGS PER DAY
IF YOU ARE PREGNANTNURSING ORTAKING ANY MEDICATIONSCONSULT YOUR DOCTOR BEFOREUSE.

STORAGE AND HANDLING

Shade and avoid direct sunlight

INACTIVE INGREDIENT

BETA CAROTENE,CITRIC ACID,GLUCOSE SYRUP, FD&C RED NO. 40, SOY LECITHIN, SUCROSE, SODIUM ASCORBATE